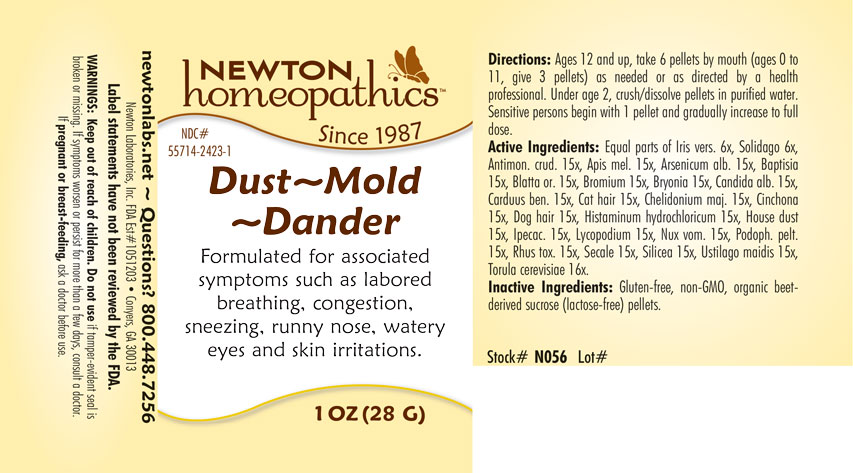 DRUG LABEL: Dust-Mold-Dander
NDC: 55714-2423 | Form: PELLET
Manufacturer: Newton Laboratories, Inc.
Category: homeopathic | Type: HUMAN OTC DRUG LABEL
Date: 20250206

ACTIVE INGREDIENTS: HOUSE DUST 15 [hp_X]/1 g; IRIS VERSICOLOR ROOT 6 [hp_X]/1 g; ANTIMONY TRISULFIDE 15 [hp_X]/1 g; APIS MELLIFERA 15 [hp_X]/1 g; ARSENIC TRIOXIDE 15 [hp_X]/1 g; BAPTISIA TINCTORIA ROOT 15 [hp_X]/1 g; BLATTA ORIENTALIS 15 [hp_X]/1 g; BROMINE 15 [hp_X]/1 g; BRYONIA ALBA ROOT 15 [hp_X]/1 g; CANDIDA ALBICANS 15 [hp_X]/1 g; CENTAUREA BENEDICTA 15 [hp_X]/1 g; FELIS CATUS HAIR 15 [hp_X]/1 g; CHELIDONIUM MAJUS 15 [hp_X]/1 g; CINCHONA OFFICINALIS BARK 15 [hp_X]/1 g; CANIS LUPUS FAMILIARIS HAIR 15 [hp_X]/1 g; HISTAMINE DIHYDROCHLORIDE 15 [hp_X]/1 g; IPECAC 15 [hp_X]/1 g; LYCOPODIUM CLAVATUM SPORE 15 [hp_X]/1 g; STRYCHNOS NUX-VOMICA SEED 15 [hp_X]/1 g; PODOPHYLLUM 15 [hp_X]/1 g; TOXICODENDRON PUBESCENS LEAF 15 [hp_X]/1 g; CLAVICEPS PURPUREA SCLEROTIUM 15 [hp_X]/1 g; SILICON DIOXIDE 15 [hp_X]/1 g; USTILAGO MAYDIS 15 [hp_X]/1 g; SACCHAROMYCES CEREVISIAE 16 [hp_X]/1 g; SOLIDAGO VIRGAUREA FLOWERING TOP 6 [hp_X]/1 g
INACTIVE INGREDIENTS: SUCROSE

Dust 2423P

INDICATIONS & USAGE SECTION

Formulated for associated symptoms such as labored breathing, congestion, sneezing, runny nose, watery eyes and skin irritations,

DOSAGE & ADMINISTRATION SECTION

Ages 12 and up, take 6 pelletsby mouth (ages 0 to 11, give 3 pellets) as needed or as directed by a health professional. Sensitive persons begin with 1 pellet and gradually increase to full dose.

OTC - ACTIVE INGREDIENT SECTION

Equal parts of Iris versicolor 6x, Solidago virgaurea 6x, Antimonium crudum 15x, Apis mellifica 15x, Arsenicum album 15x, Baptisia tinctoria 15x, Blatta orientalis 15x, Bromium 15x, Bryonia 15x, Candida albicans 15x, Carduus benedictus 15x, Cat hair 15x, Chelidonium majus 15x, Cinchona officinalis 15x, Dog hair 15x, Histaminum hydrochloricum 15x, House dust 15x, Ipecacuanha 15x, Lycopodium clavatum 15x, Nux vomica 15x, Podophyllum peltatum 15x, Rhus toxicodendron 15x, Secale cornutum 15x, Silicea 15x, Ustilago maidis 15x, Torula cerevisiae 16x.

OTC - PURPOSE SECTION

Formulated for associated symptoms such as labored breathing, congestion, sneezing, runny nose, watery eyes and skin irritations.

INACTIVE INGREDIENT SECTION

Inactive Ingredients: Gluten-free, non-GMO, organic beet-derived sucrose (lactose-free) pellets.

QUESTIONS SECTION

newtonlabs.net - Questions? 800.448.7256

Newton Laboratories, Inc. FDA Est # 1051203 Conyers, GA 30013

WARNINGS SECTION

WARNINGS: Keep out of reach of children. Do not use if tamper-evident seal is broken or missing. If symptoms worsen or persist for more than a few days, consult a doctor. If pregnant or breast-feeding, ask a doctor before use.

OTC - PREGNANCY OR BREAST FEEDING SECTION

If pregnant or breast-feeding, ask a doctor before use.

OTC - KEEP OUT OF REACH OF CHILDREN SECTION

Keep out of reach of children.